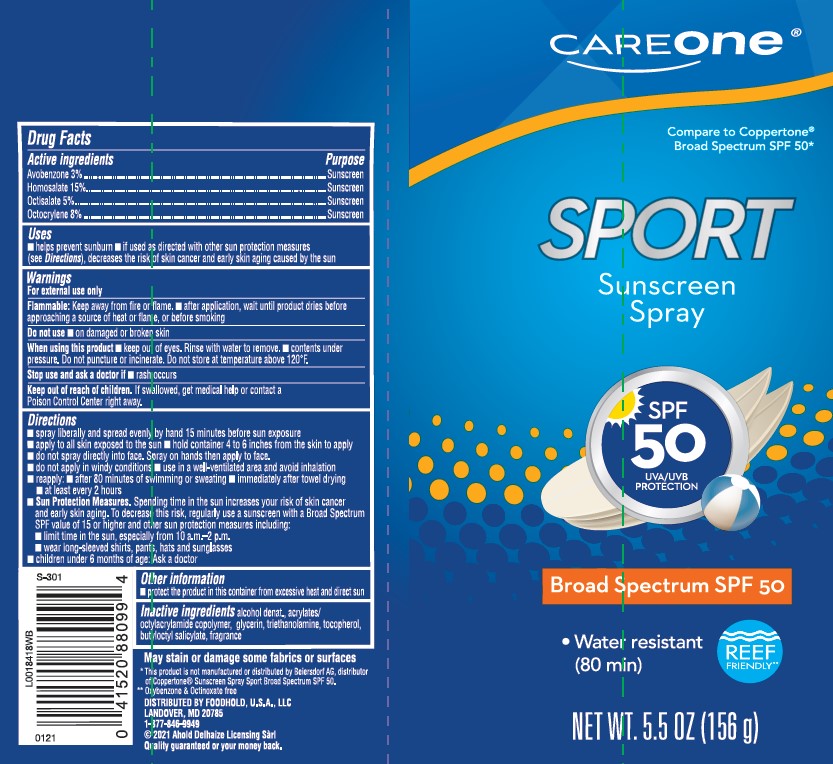 DRUG LABEL: sunscreen
NDC: 72476-938 | Form: SPRAY
Manufacturer: Retail Business Services, LLC
Category: otc | Type: HUMAN OTC DRUG LABEL
Date: 20260206

ACTIVE INGREDIENTS: AVOBENZONE 30 mg/1 g; HOMOSALATE 150 mg/1 g; OCTISALATE 50 mg/1 g; OCTOCRYLENE 80 mg/1 g
INACTIVE INGREDIENTS: ALCOHOL; STEAROXYTRIMETHYLSILANE; GLYCERIN; TROLAMINE; TOCOPHEROL; BUTYLOCTYL SALICYLATE

Care One 938.002/938AB
Sport Sunscreen Spray SPF 50

active ingredients

Avobenzone 3%
Homosalate 15%
Octisalate 5%
Octocrylene 8%

purpose

sunscreen

uses

■ helps prevent sunburn

■ if used as directed with other sun protection measures (see Directions), decreases the risk of skin cancer and early skin aging caused by the sun

warnings

For external use only

Flammable

Keep away from fire or flame.

- after application, wait until product dries before approacing a souce of heat or flame, or before smoking

do not use

- on damaged or broken skin

When using this product

- keep out of eyes. Rinse with water to remove.
- contents under pressure. Do not puncture or incinerate. Do not store at temperature above 120ºF.

stop use and ask a doctor if

- rash occurs

keep out of reach of children

if swallowed, get medical help or contact a Poison Conrol Center right away

direction

■ spray liberally and spread evenly by hand 15 minutes before sun exposure
■ apply to all skin exposed to the sun
■ hold container 4 to 6 inches from the skin to apply
■ do not spray directly into face. Spray on hands then apply to face.
■ do not apply in windy conditions
■ use in a well-ventilated area and avoid inhalation
■ reapply:
■ after 80 minutes of swimming or sweating
■ immediately after towel drying
■ at least every 2 hours
■ Sun Protection Measures. Spending time in the sun increases your risk of skin cancer and early skin aging. To decrease this risk, regularly use a sunscreen with a Broad Spectrum SPF value of 15 or higher and other sun protection measures including:
■ limit time in the sun, especially from 10 a.m.–2 p.m.
■ wear long-sleeved shirts, pants, hats and sunglasses
■ children under 6 months of age: Ask a doctor

other information

- protect the product in this container from excessive heat and direct sun

inactive ingredients

alcohol denat., acrylates/octylacrylamide copolymer, glycerin, triethanolamine, tocopherol, butyloctyl salicylate, fragrance

ADVERSE REACTION

May stain or damage some fabrics of surfaces

*This product is not manufactured or distributed by Beiersdorf AG, distributor of Coppertone®Sunscreen Spray Sport Broad Spectrum SPF 50.

**Oxybenzone & Octinoxate free

Distributed by: Foodhold, USA, LLC,

Landover, MD 20785

1-877-846-9949

2021 Ahold Delhaize Licensing Sarl

Quality guaranteed or your money back.

principal display panel

CARE ONE®

Compare to Coppertone®Broad Spectrum SPF 50*

SPORT

Sunscreen

Spray

SPF 50

UVA/UVB PROTECTION

Broad Spectrum SPF 50

- Water resistant (80 min)

REEF FRIENDLY**

NET WT. 5.5 OZ (156 g)